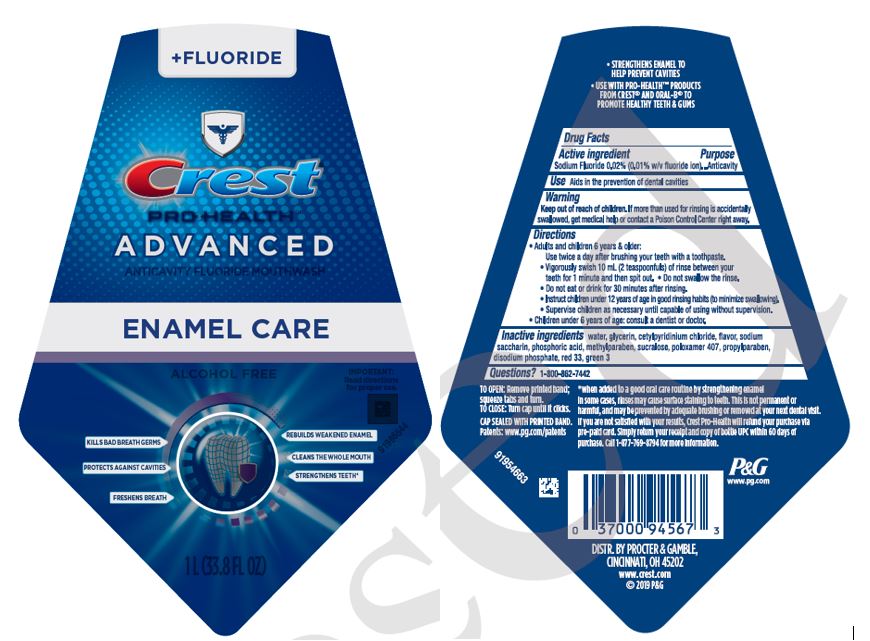 DRUG LABEL: Crest Pro-Health Advanced
NDC: 69423-745 | Form: RINSE
Manufacturer: The Procter & Gamble Manufacturing Company
Category: otc | Type: HUMAN OTC DRUG LABEL
Date: 20250806

ACTIVE INGREDIENTS: SODIUM FLUORIDE 0.02 g/20 mL
INACTIVE INGREDIENTS: WATER; GLYCERIN; HYDROGEN PEROXIDE; SUCRALOSE; POLOXAMER 407

Crest®Pro-Health™
Advanced
Enamel Care

Drug Facts

Active ingredient

Sodium Fluoride 0.02% (0.01 w/v fluoride ion)

Purpose

Anticavity

Uses

Aids the prevention of dental cavities

Warnings

Keep out of reach of children under 12 years of age.If more than used for rinsing is accidentally swallowed, get medical help or contact a Poison Control Center right away.

Directions

- Use twice a day after brushing your teeth with toothpaste.
- Vigorously swish 10mL (2 teaspoonfuls) of rinse between your teeth for 1 minute and then spit out.
- Do not swallow the rinse.
- Do not eat or drink for 30 minutes after rinsing.
- Instruct children under 12 years of age in good rinsing habits (to minimize swallowing).
- Supervise children as necessary until capable of using without supervision.
- Children under 6 years of age: consult a dentist or doctor.

Inactive ingredients

water, glycerin, cetylpyridinium chloride, flavor, sodium saccharin, phosphoric acid, methylparaben, sucralose, poloxamer 407, propylparaben, disodium phosphate, red 33, green 3

Questions?

1–800–862-7442

Dist. by Procter & Gamble,
Cincinnati OH 45202

PRINCIPAL DISPLAY PANEL - 473 mL Bottle Label

+FLUORIDE

Crest

PRO-HEALTH

ADVANCED

ANTICAVITY FLUORIDE MOUTHWASH

ENAMEL CARE

ALCOHOL FREE

IMPORTANT:

Read directions

for proper use.

KILLS BAD BREATH GERMS

PROTECTS AGAINST CAVITIES

FRESHENDS BREATH

REBUILDS WEAKENED ENAMEL

CLEANS THE WHOLE MOUTH

STRENGTHENS TEETH

1L (33.8 FL OZ)